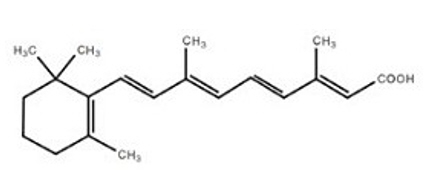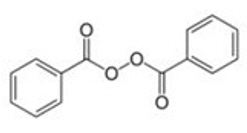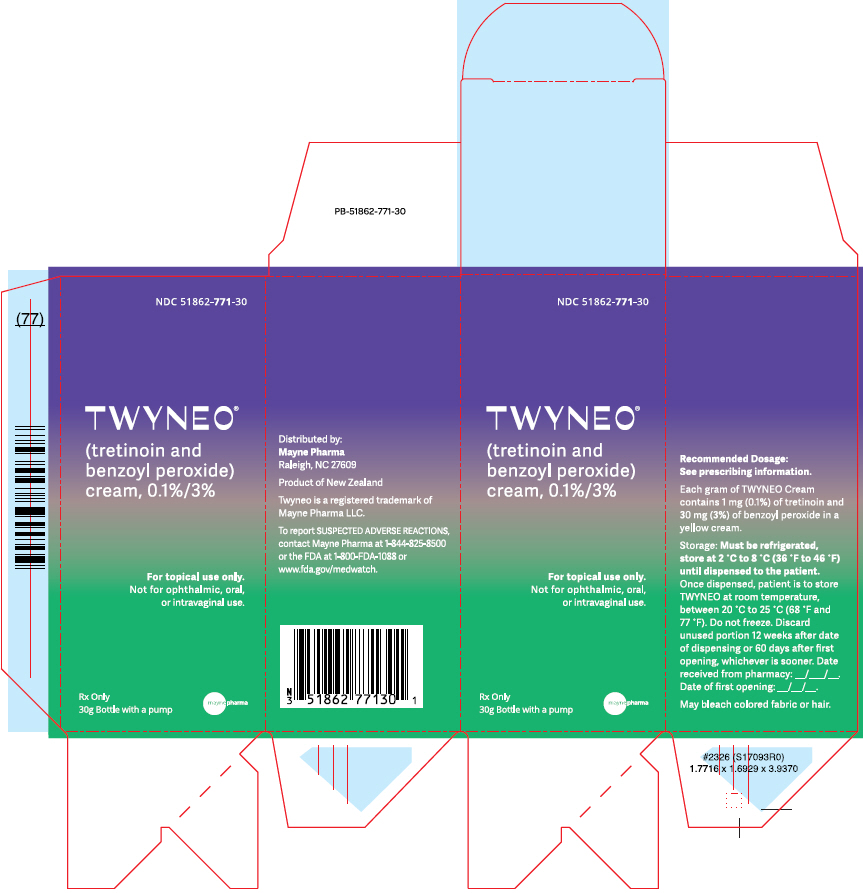 DRUG LABEL: Twyneo
NDC: 51862-771 | Form: CREAM
Manufacturer: Mayne Pharma Commercial LLC
Category: prescription | Type: HUMAN PRESCRIPTION DRUG LABEL
Date: 20250811

ACTIVE INGREDIENTS: Benzoyl Peroxide 30 mg/1 g; Tretinoin 1 mg/1 g
INACTIVE INGREDIENTS: ANHYDROUS CITRIC ACID; BUTYLATED HYDROXYTOLUENE; CARBOMER HOMOPOLYMER TYPE C (ALLYL PENTAERYTHRITOL CROSSLINKED); CETRIMONIUM CHLORIDE; CETYL ALCOHOL; CYCLOMETHICONE; EDETATE DISODIUM; GLYCERIN; HYDROCHLORIC ACID; IMIDUREA; LACTIC ACID, L-; POLYOXYL 100 STEARATE TYPE I; GLYCERYL MONO- AND DIPALMITOSTEARATE; POLYQUATERNIUM-7 (70/30 ACRYLAMIDE/DADMAC; 1600000 MW); WATER; SILICON DIOXIDE; SODIUM HYDROXIDE; SQUALANE; TETRAETHYL SILICATE; WHITE WAX

HIGHLIGHTS OF PRESCRIBING INFORMATION

These highlights do not include all the information needed to use TWYNEO safely and effectively. See full prescribing information for TWYNEO.
TWYNEO® (tretinoin and benzoyl peroxide) cream, 0.1%/3%, for topical use.
Initial U.S. Approval: 2021

1 INDICATIONS AND USAGE

TWYNEO is a combination tretinoin, a retinoid, and benzoyl peroxide indicated for the topical treatment of acne vulgaris in adults and pediatric patients 9 years of age and older. (1)

2 DOSAGE AND ADMINISTRATION

- Apply a thin layer of TWYNEO to the affected areas once daily. (2)
- Avoid contact with eyes, lips, paranasal creases, and mucous membranes. (2)
- Wash hands after application. (2)
- Not for oral, ophthalmic, or intravaginal use. (2)

3 DOSAGE FORMS AND STRENGTHS

Cream, 0.1% tretinoin/3% benzoyl peroxide (3)

4 CONTRAINDICATIONS

History of serious hypersensitivity reaction to benzoyl peroxide or any component of TWYNEO. (4)

5 WARNINGS AND PRECAUTIONS

- Hypersensitivity: Severe hypersensitivity reactions, including anaphylaxis and angioedema, have been reported with use of benzoyl peroxide products. (4, 5.1)
- Skin Irritation: Pain, dryness, exfoliation, erythema, and irritation may occur with use of TWYNEO. Avoid application of TWYNEO to cuts abrasions, eczematous or sunburned skin. (5.2)
- Photosensitivity: Minimize unprotected exposure to sunlight and sunlamps. Use sunscreen and protective clothing when sun exposure cannot be avoided. (5.3)

6 ADVERSE REACTIONS

The most common adverse reactions (incidence ≥ 1%) are pain, dryness, exfoliation erythema, dermatitis, pruritus and irritation (all at the application site). (6.1)

To report SUSPECTED ADVERSE REACTIONS, contact Mayne Pharma. at 1-844-825-8500 or FDA at 1-800-FDA-1088 or www.fda.gov/medwatch.

FULL PRESCRIBING INFORMATION

1 INDICATIONS AND USAGE

TWYNEO is indicated for the topical treatment of acne vulgaris in adults and pediatric patients 9 years of age and older.

2 DOSAGE AND ADMINISTRATION

- Apply a thin layer of TWYNEO to the affected areas once daily on clean and dry skin. Avoid contact with the eyes, lips, paranasal creases, and mucous membranes.
- Wash hands after application.
- TWYNEO is for topical use only. TWYNEO is not for oral, ophthalmic, or intravaginal use.

3 DOSAGE FORMS AND STRENGTHS

Cream, 0.1%/3%: Each gram of TWYNEO contains 1mg (0.1%) of tretinoin and 30 mg (3%) of benzoyl peroxide in a yellow cream in a 30-gram bottle with a pump.

4 CONTRAINDICATIONS

TWYNEO is contraindicated in patients with a history of hypersensitivity reaction to benzoyl peroxide or any components of TWYNEO [see Warnings and Precautions (5.1)].

5 WARNINGS AND PRECAUTIONS

5.1 Hypersensitivity

Hypersensitivity reactions, including anaphylaxis, angioedema, and urticaria, have been reported with the use of benzoyl peroxide products. If a serious hypersensitivity reaction occurs, discontinue TWYNEO immediately and initiate appropriate therapy.

5.2 Skin Irritation

Patients using TWYNEO may experience application site dryness, pain, exfoliation, erythema, dermatitis, pruritis, and irritation [see Adverse Reactions (6.1)]. Depending upon the severity of these adverse reactions, instruct patients to use a moisturizer, reduce the frequency of the application of TWYNEO, or discontinue use. Avoid application of TWYNEO to cuts, abrasions, eczematous, or sunburned skin.

5.3 Photosensitivity

TWYNEO may increase sensitivity to ultraviolet light. Minimize or avoid exposure to natural or artificial sunlight (tanning beds or UVA/B treatment) while using TWYNEO. Instruct patients to implement sun protection measures (e.g., sunscreen and loose- fitting clothes) when sun exposure cannot be avoided. Discontinue TWYNEO at the first evidence of sunburn.

6 ADVERSE REACTIONS

6.1 Clinical trials experience

The following adverse reactions are discussed in greater detail elsewhere in the labeling:

- Hypersensitivity [see Warnings and Precautions (5.1)]
- Skin Irritation [see Warnings and Precautions (5.2)]

Because clinical trials are conducted under widely varying conditions, adverse reaction rates are observed in the clinical trials of a drug cannot be directly compared to rates in the clinical trials of another drug and may not reflect the rates observed in practice.

In two multicenter, randomized, double-blind, vehicle-controlled trials (Trial 1 and 2), 832 subjects 9 years of age and older with facial acne vulgaris applied TWYNEO (N=555) or vehicle (N=277) daily for 12 weeks. The majority of subjects were White (73%) and female (59%).

Approximately 33% were Hispanic/Latino, and 46% were younger than 18 years of age. Adverse reactions reported in ≥ 1.0% of subjects treated with TWYNEO (and for which the rate exceeded the rate for vehicle), as well as the corresponding rates reported in subjects treated with vehicle are presented in Table 1.

Table 1: Adverse Reactions Reported by ≥ 1% of Subjects with Facial Acne Vulgaris Treated with TWYNEO and More Frequently than Vehicle in Trials 1 and 2
 | TWYNEO Cream (N = 555) n (%) | Vehicle Cream (N = 277) n (%)
Application Site Pain [Application site pain defined as application site stinging, burning or pain.] | 59 (10.6) | 1 (0.4)
Application Site Dryness | 27 (4.9) | 1 (0.4)
Application Site Exfoliation | 23 (4.1) | 0
Application Site Erythema | 22 (4.0) | 0
Application Site Dermatitis | 7 (1.3) | 1 (0.4)
Application Site Pruritus | 7 (1.3) | 0
Application Site Irritation | 6 (1.1) | 1 (0.4)

Local tolerability evaluations were conducted at each study visit in the clinical trial by assessment of erythema, scaling, pigmentation, dryness, itching, burning, and stinging. Table 2 presents the active assessment of the signs and symptoms of local facial tolerability at Week 12 in subjects treated with TWYNEO.

Table 2. Facial Cutaneous Tolerability Assessment at Week 12 in Subjects with Acne Vulgaris Treated with TWYNEO
 | TWYNEO (N=494 [The denominators for calculating the percentages were 494 of 555 subjects treated with TWYNEO and 264 of 277 subjects treated with vehicle in these trials who had cutaneous signs and local tolerability results reported at Week 12.]) (%) |  |  | Vehicle (N = 264) (%)
 | Mild | Moderate | Severe | Mild | Moderate | Severe
Erythema | 33.0 | 6.9 | 0.2 | 26.9 | 8.0 | 0
Pigmentation | 27.3 | 6.3 | 0.4 | 26.5 | 4.5 | 0
Dryness | 22.3 | 5.3 | 0.4 | 16.7 | 2.3 | 0
Scaling | 16.4 | 2.6 | 0 | 12.9 | 0.8 | 0
Burning | 5.9 | 2.2 | 0 | 3.4 | 0.8 | 0
Itching | 11.1 | 1.8 | 0 | 8.7 | 2.7 | 0
Stinging | 5.3 | 0.2 | 0 | 1.9 | 1.1 | 0

Local tolerability scores for erythema, scaling, dryness, itching, burning, and stinging rose during the first two weeks of treatment and decreased thereafter.

6.2 Postmarketing Experience

The following adverse reactions have been identified during use of benzoyl peroxide. Because these reactions are reported voluntarily from a population of uncertain size, it is not always possible to reliably estimate their frequency or establish a causal relationship to drug exposure.

Immune System Disorders: Anaphylaxis, angioedema and urticaria

8 USE IN SPECIFIC POPULATIONS

8.1 Pregnancy

Risk Summary

Available data from published observational studies of topical tretinoin in pregnant women have not established a drug-associated risk of major birth defects, miscarriage, or adverse maternal or fetal outcomes. Studies conducted with topical benzoyl peroxide have not demonstrated systemic absorption and maternal use is not expected to result in fetal exposure to benzoyl peroxide. There are no data on TWYNEO use in pregnant women.

There are reports of major birth defects reported with maternal use of topical tretinoin similar to those seen in infants exposed to oral retinoids, but these case reports do not establish a pattern or association with tretinoin-related embryopathy (see Data).

Animal reproductive studies have not been conducted with TWYNEO or benzoyl peroxide. Topical administration of tretinoin to pregnant rats during organogenesis was associated with malformations (craniofacial abnormalities [hydrocephaly], asymmetrical thyroids, variations in ossification, and increased supernumerary ribs) at doses greater than 1 mg tretinoin/kg/day, approximately 5 times the maximum recommended human dose (MRHD) based on body surface area (BSA) comparison and assuming 100% absorption. Oral administration of tretinoin to pregnant cynomolgus monkeys during organogenesis was associated with malformations at 10 mg/kg/day (approximately 100 times the MRHD based on BSA comparison and assuming 100% absorption) (see Data).

The background risk of major birth defects and miscarriage for the indicated population is unknown. All pregnancies have a background risk of major birth defects, loss and other adverse outcomes. The background risk in the U.S. general population of major birth defects is 2 to 4% of miscarriage is 15 to 20% of clinically recognized pregnancies.

Data

Human Data

While available studies cannot definitively establish the absence of risk, published data from multiple prospective controlled observational studies on the use of topical tretinoin products during pregnancy have not identified an association with topical tretinoin and major birth defects or miscarriage. The available studies have methodologic limitations, including small sample size and in some cases, lack of physical exam by an expert in birth defects. There are published case reports of infants exposed to topical tretinoin during the first trimester that describe major birth defects similar to those seen in infants exposed to oral retinoids; however, no pattern of malformations has been identified and no causal association has been established in these cases. The significance of these spontaneous reports in terms of risk to the fetus is not known.

Animal Data

For purposes of comparison of the animal exposure to human exposure, the MRHD is defined as 1.5 g of TWYNEO (containing 0.1% tretinoin) applied daily to a 60-kg person (0.03 mg tretinoin/kg body weight).

Topical tretinoin embryofetal development studies have generated equivocal results. There is evidence for malformations (shortened or kinked tail) after topical tretinoin administration in Wistar rats at doses greater than 1 mg/kg/day (approximately 5 times the MHRD based on BSA comparison and assuming 100% absorption). Anomalies (humerus: short 13%, bent 6%, or parietal incompletely ossified 14%) have also been reported when 10 mg/kg/day (approximately 50 times the MRHD based on BSA comparison and assuming 100% absorption) was topically applied to pregnant rats during organogenesis. Increased incidence of domed head and hydrocephaly, typical of retinoid-induced fetal malformations were noted in New Zealand White rabbits administered topical doses greater than 0.2 mg/kg/day (2.2 times the MRHD based on BSA comparison and assuming 100% absorption).

Oral tretinoin induced malformations in rats, mice, hamsters, and nonhuman primates when administered during the period of organogenesis. Fetal malformations were observed when tretinoin was orally administered to pregnant Wistar rats during organogenesis. It was teratogenic and fetotoxic in Wistar rats when given orally or topically in doses greater than 1 mg/kg/day (approximately 5 times the MRHD based on BSA comparison and assuming 100% absorption). In the cynomolgus monkey, fetal malformations were reported when an oral dose of 10 mg/kg/day was administered to pregnant monkeys during organogenesis (approximately 100 times the MRHD based on BSA comparison and assuming 100% absorption). No fetal malformations were observed at an oral dose of 5 mg/kg/day (approximately 50 times the MRHD based on BSA comparison and assuming 100% absorption). Increased skeletal variations were observed at all doses, and a dose-related increase in embryo lethality and abortion was reported in this study. Similar results have also been reported in pigtail macaques. Oral tretinoin has been shown to be fetotoxic in rats when administered at a dose of 2.5 mg/kg/day (13 times the MRHD based on BSA comparison and assuming 100% absorption). Topical tretinoin has been shown to be fetotoxic in rabbits when administered at a dose of 0.5 mg/kg/day (5 times the MRHD based on BSA comparison and assuming 100% absorption).

8.2 Lactation

Risk Summary

There are no data on the presence of benzoyl peroxide and tretinoin or its metabolites in human milk, the effects on the breastfed infant, or the effects on milk production. It is not known whether topical administration of tretinoin could result in sufficient systemic absorption to produce detectable concentrations in human milk. The developmental and health benefits of breastfeeding should be considered along with the mother's clinical need for TWYNEO and any potential adverse effects on the breastfed child from TWYNEO or from the underlying maternal condition.

8.4 Pediatric Use

The safety and effectiveness of TWYNEO for the topical treatment of acne vulgaris have been established in pediatric patients 9 years of age and older based on evidence from two multicenter, randomized, double-blind, parallel-group, vehicle-controlled, 12-week clinical trials and an open-label pharmacokinetic study. A total of 283 pediatric subjects 9 years of age and older received TWYNEO in the clinical studies [see Clinical Pharmacology (12.3) and Clinical Studies (14)].

The safety and effectiveness of TWYNEO in pediatric patients below 9 years of age have not been established.

8.5 Geriatric Use

Clinical trials of TWYNEO did not include sufficient numbers of subjects 65 years of age and older to determine whether they respond differently than younger subjects.

11 DESCRIPTION

TWYNEO (tretinoin and benzoyl peroxide) cream is a yellow cream for topical use. Each gram of TWYNEO contains 1 mg (0.1%) of tretinoin and 30 mg (3%) of benzoyl peroxide. Tretinoin is a retinoid and benzoyl peroxide is an oxidizing agent.

The chemical name for tretinoin is all-trans-retinoic acid, also known as (all-E)-3,7- dimethyl-9-(2,6,6-trimethyl-1-cyclohexen-1-yl)-2,4,6,8-nonatetraenoic acid. Tretinoin has the following structural formula:

Molecular Formula: C20H28O2

Molecular Weight: 300.44

The chemical name for benzoyl peroxide is benzoyl benzenecarboperoxoate. Benzoyl peroxide has the following structural formula:

Molecular Formula: C14H10O4

Molecular Weight: 242.23

The formulation of TWYNEO uses silica (silicon dioxide) core shell structures to separately micro-encapsulate tretinoin crystals and benzoyl peroxide crystals enabling inclusion of the two active ingredients in the. TWYNEO contains the following inactive ingredients: anhydrous citric acid, butylated hydroxytoluene, carbomer homopolymer type C, cetrimonium chloride, cetyl alcohol, cyclomethicone, edetate disodium, glycerin, hydrochloric acid, imidurea, (S)lactic acid, macrogol stearate, mono and di-glycerides, polyquaternium-7, purified water, silicon dioxide, sodium hydroxide, squalane, tetraethyl ortho silicate and white wax.

12 CLINICAL PHARMACOLOGY

12.1 Mechanism of Action

Benzoyl peroxide is an oxidizing agent with bactericidal and keratolytic effects, but the precise mechanism of action is unknown. Tretinoin is a metabolite of vitamin A that binds with high affinity to specific retinoic acid receptors located in both the cytosol and nucleus. Tretinoin activates three members of the retinoic acid (RAR) nuclear receptors (RARα , RARβ, RARγ) which act to modify gene expression, subsequent protein synthesis, and epithelial cell growth and differentiation. It has not been established whether the clinical effects of tretinoin are mediated through activation of retinoic acid receptors, and/or other mechanisms.

Although the exact mode of action of tretinoin in acne treatment is unknown, current evidence suggests that topical tretinoin decreases cohesiveness of follicular epithelial cells with decreased microcomedo formation. Additionally, tretinoin stimulates mitotic activity and increased turnover of follicular epithelial cells causing extrusion of the comedones.

12.2 Pharmacodynamics

Pharmacodynamics of TWYNEO in the treatment of acne vulgaris are unknown.

12.3 Pharmacokinetics

The systemic exposure of benzoyl peroxide was not assessed. Benzoyl peroxide is absorbed by skin where it is converted to benzoic acid and eliminated in the urine.

Plasma concentrations of tretinoin and its major metabolites were evaluated in 35 subjects in an open-label, randomized, pharmacokinetic (PK) study. Subjects 9 years of age and older with acne vulgaris applied a mean dose of 1.9 g TWYNEO to the skin of the face, shoulders, upper back and upper chest once daily for 14 days.

Steady-state PK characteristics were determined from samples drawn on Day 14. The mean baseline corrected Cmax and AUC0-24 of tretinoin and its metabolites after once daily application of TWYNEO for 14 days are provided in Table 3. No detectable levels of the metabolites a l-trans 4-keto retinoic acid and 9-cis retinoid acid were found in subjects treated with TWYNEO.

Table 3: Pharmacokinetics of Tretinoin and its Major Metabolites When Treated with TWYNEO in Subjects 9 Years of Age and Older With Acne Vulgaris for 14 Days
Age Group (years) | n | Compound | Mean(± SD) Cmax (ng/mL) | Mean(± SD) AUC0-24 (ng-h/mL)
≥ 18 years of age | 12 | tretinoin | 0.15 ± 0.17 | 0.63 ± 0.95
 |  | 4-keto 13-cis RA | 0.27 ± 0.29 | 2.88 ± 3.61
 |  | 13-cis RA | 0.21 ± 0.19 | 1.99 ± 2.90
12 to 17 | 15 | tretinoin | 0.19 ± 0.18 | 1.56 ± 1.97
 |  | 4-keto 13-cis RA | 0.32 ± 0.28 | 2.39 ± 3.05
 |  | 13-cis RA | 0.28 ± 0.35 | 1.79 ± 2.79
9 to 11 | 8 | tretinoin | 0.18 ± 0.22 | 2.06 ± 3.96
 |  | 4-keto 13-cis RA | 0.34 ± 0.36 | 2.89 ± 3.17
 |  | 13-cis RA | 0.13 ± 0.09 | 0.96 ± 1.36

13 NONCLINICAL TOXICOLOGY

13.1 Carcinogenesis, Mutagenesis, Impairment of Fertility

Carcinogenicity, mutagenicity, and impairment of fertility studies were not conducted with TWYNEO.

Benzoyl peroxide

The role of benzoyl peroxide as a tumor promoter has been well established in several animal species; however the significance of this finding in humans is unknown.

No significant increase in tumor formation was observed in rats treated topically with 15 to 25% benzoyl peroxide carbopol gel (5 to 8 times the concentration of benzoyl peroxide in TWYNEO) for two years. Similar results were obtained in mice topically treated with 25% benzoyl peroxide carbopol gel for 56 weeks followed by intermittent treatment with 15% benzoyl peroxide gel for the rest of the two-year study period, and in mice treated topically with 5% benzoyl peroxide carbopol gel for two years.

Bacterial mutagenicity assays (Ames test) conducted with benzoyl peroxide have provided mixed results. Mutagenic potential was observed in a few studies but not in a majority of investigations. Benzoyl peroxide has been found to cause DNA strand breaks in a variety of mammalian ce l types and to cause sister chromatid exchanges in Chinese hamster ovary cells.

Fertility studies were not conducted with benzoyl peroxide.

Tretinoin

In a 91-week dermal study, CD-1 mice were administered 0.017% and 0.035% formulations of tretinoin, cutaneous squamous cell carcinomas and papillomas in the treatment area were observed in some female mice. A dose-related incidence of liver tumors in male mice was observed at those same doses. The maximum systemic doses associated with the administered 0.017% and 0.035% formulations are 0.5 and 1.0 mg/kg/day, respectively. These doses are 1.3 and 2.7 times the MRHD based on BSA comparison and assuming 100% absorption. The biological significance of these findings is not clear because they occurred at doses that exceeded the dermal maximally tolerated dose (MTD) of tretinoin and because they were within the background natural occurrence rate for these tumors in this strain of mice. There was no evidence of carcinogenic potential when 0.025 mg/kg/day of tretinoin was administered topically to mice (0.07 times the MRHD based on BSA comparison and assuming 100% absorption). The genotoxic potential of tretinoin was evaluated in an in vitro bacterial reversion test and an in vivo rat micronucleus assay, both of which were negative.

In dermal fertility studies of another tretinoin formulation in rats, slight (not statistically significant) decreases in sperm count and motility were seen at 0.5 mg/kg/day (approximately 2.7 times the MRHD based on BSA comparison and assuming 100% absorption), and slight (not statistically significant) increases in the number and percent of nonviable embryos in females treated with 0.25 mg/kg/day and above (1.3 times MRHD based on BSA comparison and assuming 100% absorption) were observed.

14 CLINICAL STUDIES

The safety and efficacy of TWYNEO was evaluated in the treatment of acne vulgaris in two multicenter, randomized, double-blind, vehicle-controlled trials [Trial 1 (NCT03761784), Trial 2 (NCT03761810)], which were identical in design. The trials were conducted in 858 subjects 9 years of age and older, with facial acne vulgaris who were treated once daily for 12 weeks with either TWYNEO or vehicle.

Subjects were required to have a score of moderate (3) or severe (4) on the Investigator Global Assessment (IGA), 20 to 100 inflammatory lesions (papules, pustules and nodules), 30 to 150 non-inflammatory lesions (open and closed comedones) and two or fewer facial nodules. Overall, 73% of subjects were White and 59% were female. Eighteen (18) (2%) subjects were 9 to 11 years of age, 370 (43%) subjects were 12 to 17 years of age, and 470 (55%) subjects were 18 years of age or older. At baseline, subjects had a mean inflammatory lesion count of 30.7 and a mean noninflammatory lesion count of 46.4.

Additionally, 91% of subjects had an IGA score of 3 ("moderate").

The co-primary efficacy endpoints were the absolute change from baseline in non- inflammatory lesion count, and absolute change in inflammatory lesion count at Week 12 and the proportion of subjects with IGA success at Week 12, defined as an IGA score of 0 ("clear") or 1 ("almost clear"), and at least a two-grade improvement (decrease) from baseline at Week 12. The efficacy results are provided in Table 4.

Table 4: Efficacy Results in Subjects with Acne Vulgaris at Week 12 (Trials 1 and 2)
 | Trial 1 |  | Trial 2
 | TWYNEO (N = 281) | Vehicle N = 143) | TWYNEO (N = 290) | Vehicle (N = 144)
IGA Success [Investigator Global Assessment (IGA) success was defined as an IGA score of 0 ("clear") or1 ("almost clear") with at least at two-grade reduction from baseline.] | 33.9% | 14.3% | 26.8% | 15.1%
Difference from Vehicle | 25.7% |  | 11.6%
(95% CI) | (17.1%, 34.2%) |  | (3.6%, 19.7%)
Inflammatory Lesions
Mean [Means presented in table are Least Square (LS) Means.] Absolute Change from Baseline | -21.6 | -14.8 | -16.2 | -14.1
Difference from Vehicle | -6.8 |  | -2.1
(95% CI) | (-9.1, -4.6) |  | (-3.9, -0.4)
Mean Percent Change from Baseline | -66.1% | -43.5% | -57.6% | -50.8%
Difference from Vehicle | -22.6% |  | -6.8%
(95% CI) | (-29.2%, -16.0%) |  | (-13.1%, -0.5%)
Non-Inflammatory Lesions
Mean Absolute Change from Baseline | -29.7 | -19.8 | -24.2 | -17.4
Difference from Vehicle | -9.9 |  | -6.8
(95% CI) | (-13.0, -6.8) |  | (-9.9, -3.7)
Mean Percent Change from Baseline | -61.6% | -40.9% | -54.4% | -41.5%
Difference from Vehicle | -20.7% |  | -13.0%
(95% CI) | (-27.2%, -14.2%) |  | (-19.6%, -6.4%)

16 HOW SUPPLIED/STORAGE AND HANDLING

How Supplied

TWYNEO (tretinoin and benzoyl peroxide) cream, 0.1%/3% is a yellow cream and is supplied as:

- 30-gram bottle with a pump, NDC 51862-771-30

Storage and Handling

- Prior to Dispensing: Store TWYNEO between 2°C to 8°C (36°F to 46°F) until dispensed to the patient.
- After Dispensing: Store TWYNEO at room temperature between 20°C to 25°C (68°F to 77°F). Discard 12 weeks after date of dispensing or 60 days after first opening, whichever is sooner.
- Do not freeze.

17 PATIENT COUNSELING INFORMATION

Advise the patient to read the FDA-approved patient labeling (Patient Information).

Hypersensitivity

Inform patients that serious hypersensitivity reactions have occurred with the use of benzoyl peroxide products. If a patient experiences a serious hypersensitivity reaction, instruct patient to discontinue TWYNEO immediately and seek medical help [see Warnings and Precautions (5.1)].

Skin Irritation

Inform patients that TWYNEO may cause irritation such as erythema, dryness, stinging or burning. Advise the patient to use a moisturizer for irritation. [see Warnings and Precautions (5.2)].

Photosensitivity

Advise patients to minimize unprotected exposure to sunlight and sunlamps; recommend the use of sunscreen products and protective apparel (e.g., hat) over treated areas when sun exposure cannot be avoided. [see Warnings and Precautions (5.3)].

Administration Instructions

Advise patients to apply TWYNEO exactly as directed in a thin layer, avoiding the eyes, lips, paranasal creases and mucous membranes and to wash hands immediately after application. Inform patients that TWYNEO may bleach hair or colored fabric [see Dosage and Administration (2)].

Discard Instructions

Instruct patients to store TWYNEO at room temperature and to discard 12 weeks after date of dispensing or 60 days after first opening, whichever is sooner. [see How Supplied/Storage and Handling (16)].

Distributed by:
Mayne Pharma
Raleigh, NC 27609
Made in New Zealand
All trademarks are the property of their respective owners

PATIENT INFORMATION

TWYNEO ® (Twye'nee oh)
(tretinoin and benzoyl peroxide)
cream, for topical use

Important: TWYNEO is for use on the skin only (topical). Do not use TWYNEO in your mouth, eyes, or vagina.

What is TWYNEO?

TWYNEO is a prescription medicine used on the skin (topical) to treat acne vulgaris in adults and children 9 years of age and older.

It is not known if TWYNEO is safe and effective in children below 9 years of age.

Do not use TWYNEO if you have had an allergic reaction to benzoyl peroxide or any of the ingredients in TWYNEO. See the end of this leaflet for a complete list of ingredients in TWYNEO.

Before using TWYNEO, tell your healthcare provider about all of your medical conditions, including if you:

- have other skin problems, including eczema, cuts, or sunburn
- have skin sensitivity to the sun
- are pregnant or planning to become pregnant. It is not known if TWYNEO wi l harm your unborn baby.
- are breastfeeding or plan to breastfeed. It is not known if TWYNEO passes into your breast milk. Talk to your healthcare provider about the best way to feed your baby during treatment with TWYNEO.

Tell your healthcare provider about all the medicines you take, including prescription and over-the-counter medicines, vitamins, and herbal supplements.

How should I use TWYNEO?

- Use TWYNEO exactly as your healthcare provider tells you to use it.
- Apply TWYNEO to the affected areas 1 time a day.
- Apply TWYNEO on clean and dry skin.
- TWYNEO come in a bottle with a pump. Press down on (depress) the pump to dispense a small amount of TWYNEO on your fingertip. Apply a thin layer of TWYNEO to the affected areas. Avoid contact with your eyes, lips, corners of your nose, and mouth.
- Wash your hands right away after applying TWYNEO.

What should I avoid while using TWYNEO?

- Avoid using TWYNEO on skin areas with cuts, abrasions, eczema, or sunburns.
- Limit your time in sunlight. You should avoid using sunlamps, tanning beds, and ultraviolet light during treatment with TWYNEO. If you have to be in the sunlight or are sensitive to sunlight, use sunscreen and wear protective clothing or a wide- brimmed hat to cover the treated areas.
- Avoid getting TWYNEO in your hair or on colored fabric. TWYNEO may bleach hair or colored fabric.

What are the possible side effects of TWYNEO? TWYNEO may cause serious side effects including:

- Allergic reactions. Stop using TWYNEO and get medical help right away if you have any of the following symptoms during treatment with TWYNEO:
  - hives, rash or severe itching
  - swelling of your face, eyes, lips, tongue, or throat
  - trouble breathing or throat tightness
  - feeling faint, dizzy, or lightheaded
- Skin irritation. TWYNEO may cause skin irritation such as redness, scaling, peeling, dryness, pain, stinging or burning. If you develop these symptoms, your healthcare provider may tell you to use a moisturizer, decrease the number of times you
  apply TWYNEO, or completely stop treatment of TWYNEO.

The most common side effects of TWYNEO include pain, dryness, peeling, redness, swe ling, itching, and irritation at the application site.

These are not all possible side effects of TWYNEO.
Call your doctor for medical advice about side effects. You may report side effects to the FDA at 1-800-FDA-1088.
You may also report side effects to Galderma Laboratories, L.P. at 1-866-735-4137.

How should I store TWYNEO?

- Store TWYNEO at room temperature between 68°F to 77°F (20C° to 25°C).
- Throw away (discard) TWYNEO 12 weeks after the date you receive it or 60 days after first opening, whichever is sooner.
- Do not freeze.

Keep TWYNEO and all medicines out of reach of children.

General information about the safe and effective use of TWYNEO. Medicines are sometimes prescribed for purposes other than those listed in a Patient Information leaflet. Do not use TWYNEO for a condition for which it was not prescribed. Do not use TWYNEO for a condition for which it was not prescribed. Do not give TWYNEO to other people, even if they have the same symptoms that you have. It may harm them. You can ask your pharmacist or healthcare provider for information about TWYNEO that is written for health professionals.

What are the ingredients in TWYNEO?
Active Ingredients: tretinoin and benzoyl peroxide
Inactive Ingredients: anhydrous citric acid, butylated hydroxytoluene, carbomer homopolymer type C, cetrimonium chloride, cetyl alcohol, cyclomethicone, edetate disodium, glycerin, hydrochloric acid, imidurea, (S)-lactic acid, macrogol stearate, mono and di-glycerides, polyquaternium-7, purified water, silicon dioxide, sodium hydroxide, squalane, tetraethyl ortho silicate and white wax.

Distributed by:
Mayne Pharma
Raleigh, NC 27609
TWYNEO is a registered trademark of Mayne Pharma LLC.
Product of New Zealand

IN-51862-771-30

This Patient Information has been approved by the U.S. Food and Drug Administration.
Issued 02/2025

PRINCIPAL DISPLAY PANEL - 30 g Bottle Carton

NDC 51862-771-30

TWYNEO®

(tretinoin and
benzoyl peroxide)
cream, 0.1%/3%

For topical use only.
Not for ophthalmic, oral,
or intravaginal use.

Rx Only
30g Bottle with a pump

pharma